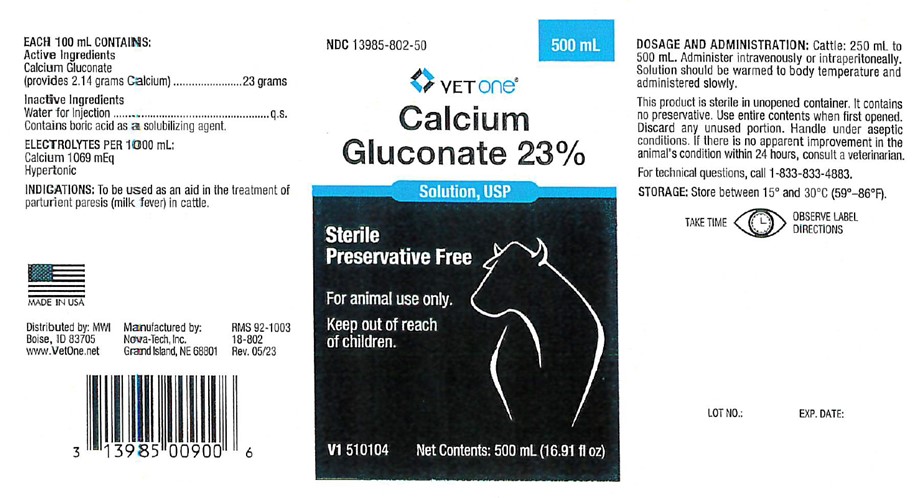 DRUG LABEL: Calcium Gluconate
NDC: 13985-802 | Form: INJECTION, SOLUTION
Manufacturer: MWI/VetOne
Category: animal | Type: OTC ANIMAL DRUG LABEL
Date: 20231227

ACTIVE INGREDIENTS: CALCIUM GLUCONATE 23 g/100 mL

Calcium Gluconate 23%

EACH 100 mL CONTAINS Active Ingredients

Calcium Gluconate
(provides 2.14 grams Calcium)...................23 grams

ELECTROLYTES PER 1000 mL:
Calcium 1069 mEq
Hypertonic

Inactive Ingredients

Water for Injection...........................................q.s.
Contains borid acid as a solubilizing agent.

INDICATIONS:

To be used as an aid in the treatment of parturient paresis (milk fever) in cattle.

INFORMATION FOR OWNERS/CAREGIVERS

Distributed by: MWI
Boise, ID 83705
(888) 694-8381
www.VetOne.net

Manufactured by: Nova-Tech, Inc.
Grand Island, NE 68801

Solution, USP

Sterile
Preservative Free

V1 510104 Net Contents: 500 mL

RMS 92-1003
18-802
Rev 05/23

LOT NO.: EXP. DATE:

KEEP OUT OF REACH OF CHILDREN

For animal use only.

Keep out of reach of children.

DOSAGE AND ADMINISTRATION:

Cattle: 250 mL to 500 mL. Administer intravenously or intraperitoneally. Solution should be warmed to body temperature and administered slowly.

This product is sterile in unopened container. It contains no preservative. Use entire contents when first opened. Discard any unused portion. Handle under aseptic conditions. If there is no apparent improvement in the animal's condition within 24 hours, consult a veterinarian.

STORAGE:

Store between 15 degrees and 30 degrees C (59 degrees - 86 degrees F).

WARNINGS AND PRECAUTIONS

TAKE TIME OBSERVE LABEL DIRECTIONS